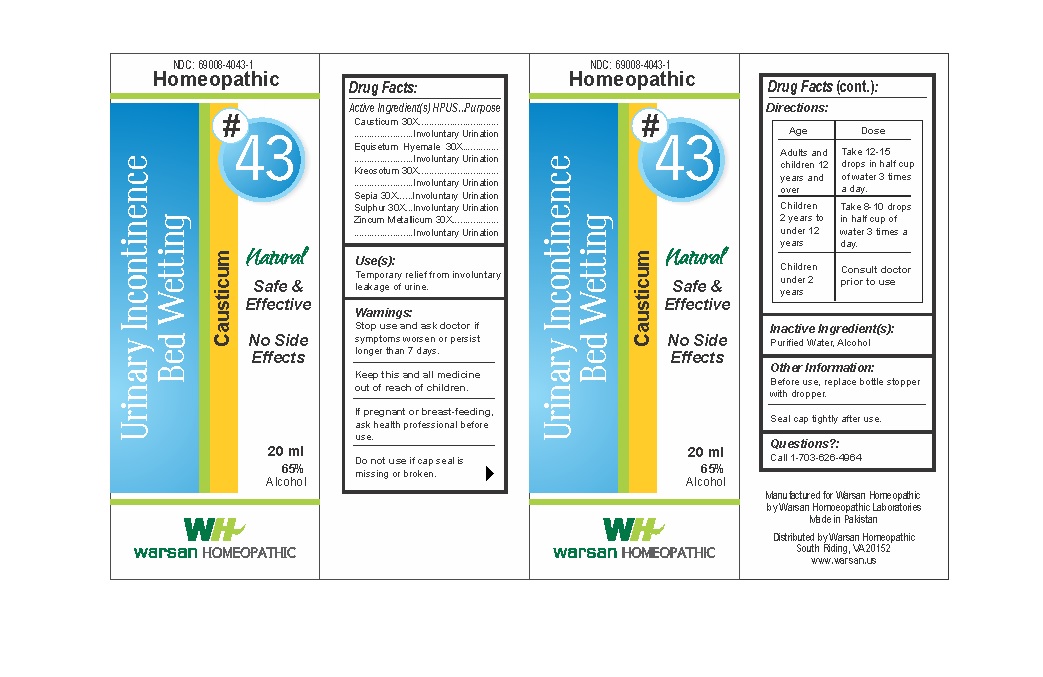 DRUG LABEL: Combination Remedy 43 - Urinary Incontinence Bed Wetting
NDC: 69008-4043 | Form: SOLUTION/ DROPS
Manufacturer: Warsan Homoeopathic Laboratories
Category: homeopathic | Type: HUMAN OTC DRUG LABEL
Date: 20171225

ACTIVE INGREDIENTS: WOOD CREOSOTE 30 [hp_X]/1 mL; SEPIA OFFICINALIS JUICE 30 [hp_X]/1 mL; CAUSTICUM 30 [hp_X]/1 mL; ZINC 30 [hp_X]/1 mL; EQUISETUM HYEMALE 30 [hp_X]/1 mL; SULFUR 30 [hp_X]/1 mL
INACTIVE INGREDIENTS: ALCOHOL; WATER

Stop use and ask doctor if symptoms worsen or persist longer than 7 days.

If pregnant or breast-feeding, ask health professional before use.

Do not use if tamper evident seal is missing or broken.

Keep out of reach of children.

ACTIVE INGREDIENT

Causticum 30X

Equisetum Hyemale 30X

Kreosotum 30X

Sepia 30X

Sulphur 30X

Zincum Metallicum 30X

PURPOSE

Temporary relief from involuntary leakage of urine.

INACTIVE INGREDIENT

Purified Water

Alcohol

DOSAGE AND ADMINISTRATION

Adults and children 12 years and older: Take 10-15 drops in half cup of water 3 times a day.

Children 2 years to under 12 years: Take 8-10 drops in half cup of water of 3 times a day.

Children under 2 years: Consult doctor prior to use.

INDICATIONS AND USAGE

Temporary relief from involuntary leakage of urine.